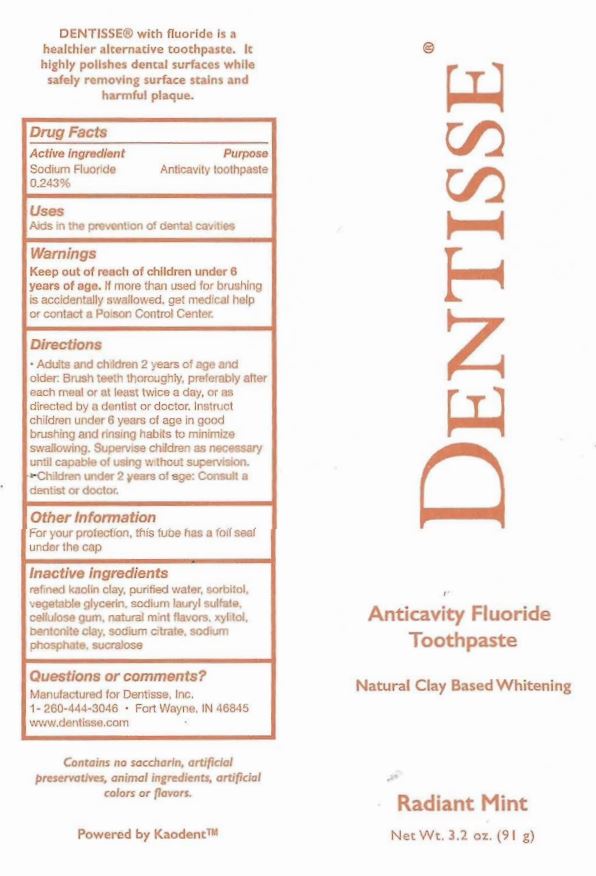 DRUG LABEL: Dentisse
NDC: 70683-0703 | Form: PASTE, DENTIFRICE
Manufacturer: Dentisse, Inc.
Category: otc | Type: HUMAN OTC DRUG LABEL
Date: 20251104

ACTIVE INGREDIENTS: SODIUM FLUORIDE 1.1 mg/1 g
INACTIVE INGREDIENTS: KAOLIN; BENTONITE; SODIUM LAURYL SULFATE; WATER; SORBITOL; GLYCERIN; CARBOXYMETHYLCELLULOSE SODIUM; SODIUM PHOSPHATE, DIBASIC; XYLITOL; SUCRALOSE; MENTHOL; SODIUM CITRATE

Dentisse

Active ingredient

Sodium Fluoride 0.243%

Purpose

Anticavity Toothpaste

Uses

Aids in the prevention of dental cavities.

Warnings

Keep out of reach of children under 6 years of age. If more than used for brushing is accidently swallowed, get medical help or contact a Poison Control Center right away.

Directions

- Adults and children 2 years of age and older Brush teeth thoroughly preferably after each meal or at least twice a day, or as directed by a dentist or doctor. Instruct children under 6 years of age in good brushing and rinsing habits to minimize swallowing. Supervise children as necessary until capable of using without supevision.
- Children under 2 years of age, constult a dentist or a doctor.

Other information

For your protection, this tube has a foil seal under the cap.

Inactive ingredients

refined kaolin clay, purified water, sorbitol, vegetable glycerin, sodium laurly sulfate, cellulose gum, natural mint flavors, xylitol, bentonite clay, sodium citrate, sodium phosphate, sucralose

Questions or comments?

Manufactured for Dentisse, Inc.

1-260-444-3046 Fort Wayne, IN 46825

www.dentisse.com

Principal Display Panel

DENTISSE ®

Anticavity Fluoride

Toothpaste

Natural Clay Based Whitening

Radiant Mint

Net Wt. 3.2 oz. (91 g)